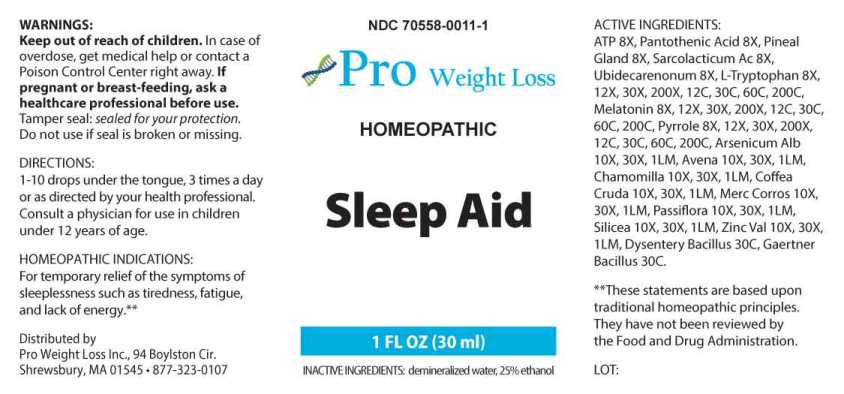 DRUG LABEL: Sleep Aid
NDC: 70558-0011 | Form: LIQUID
Manufacturer: Pro Weight Loss Inc.
Category: homeopathic | Type: HUMAN OTC DRUG LABEL
Date: 20210716

ACTIVE INGREDIENTS: ADENOSINE TRIPHOSPHATE DISODIUM 8 [hp_X]/1 mL; PANTOTHENIC ACID 8 [hp_X]/1 mL; SUS SCROFA PINEAL GLAND 8 [hp_X]/1 mL; LACTIC ACID, L- 8 [hp_X]/1 mL; UBIDECARENONE 8 [hp_X]/1 mL; TRYPTOPHAN 8 [hp_X]/1 mL; MELATONIN 8 [hp_X]/1 mL; PYRROLE 8 [hp_X]/1 mL; ARSENIC TRIOXIDE 10 [hp_X]/1 mL; AVENA SATIVA FLOWERING TOP 10 [hp_X]/1 mL; MATRICARIA CHAMOMILLA WHOLE 10 [hp_X]/1 mL; ARABICA COFFEE BEAN 10 [hp_X]/1 mL; MERCURIC CHLORIDE 10 [hp_X]/1 mL; PASSIFLORA INCARNATA FLOWERING TOP 10 [hp_X]/1 mL; SILICON DIOXIDE 10 [hp_X]/1 mL; ZINC VALERATE DIHYDRATE 10 [hp_X]/1 mL; SHIGELLA DYSENTERIAE 30 [hp_C]/1 mL; SALMONELLA ENTERICA ENTERICA SEROVAR ENTERITIDIS 30 [hp_C]/1 mL
INACTIVE INGREDIENTS: WATER; ALCOHOL

DRUG FACTS:

ACTIVE INGREDIENTS:

Adenosinum Triphosphoricum Dinatrum 8X, Pantothenic Acid 8X, Pineal Gland (Suis) 8X, Sarcolacticum Acidum 8X, Ubidecarenonum 8X, L-Tryptophan, Melatonin 8X, 12X, 30X, 200X, 12C, 30C, 60C, 200C, Pyrrole 8X, 12X, 30X, 200X, 12C, 30C, 60C, 200C , Arsenicum Album 10X, 30X, 1LM, Avena Sativa 10X, 30X, 1LM, Chamomilla 10X, 30X, 1LM, Coffea Cruda 10X, 30X, 1LM, Mercurius Corrosivus 10X, 30X, 1LM, Passiflora Incarnata 10X, 30X, 1LM, Silicea 10X, 30X, 1LM, Zincum Valerianicum 10X, 30X, 1LM, Dysentery Bacillus 30C, Gaertner Bacillus (Bach) 30C.

HOMEOPATHIC INDICATIONS:

For temporary relief of the symptoms of sleeplessness such as tiredness, fatigue, and lack of energy.**

**These statements are based upon traditional homeopathic principles. They have not been reviewed by the Food and Drug Administration.

WARNINGS:

Keep out of reach of children. In case of overdose, get medical help or contact a Poison Control Center right away.

If pregnant or breast-feeding, ask a healthcare professional before use.

Tamper seal: "Sealed for Your Protection."

Do not use if seal is broken or missing.

Keep out of reach of children. In case of overdose, get medical help or contact a Poison Control Center right away.

DIRECTIONS:

1-10 drops under the tongue, 3 times a day or as directed by your health professional. Consult a physician for use in children under 12 years of age.

HOMEOPATHIC INDICATIONS:

For temporary relief of the symptoms of sleeplessness such as tiredness, fatigue, and lack of energy.**

**These statements are based upon traditional homeopathic principles. They have not been reviewed by the Food and Drug Administration.

INACTIVE INGREDIENTS:

demineralized water, 25% ethanol

QUESTIONS:

Distributed by

Pro Weight Loss Inc., 94 Boylston Cir.

Shrewsbury, MA 01545 • 877-323-0107

PACKAGE LABEL DISPLAY:

NDC 70558-0011-1

Pro Weight Loss

HOMEOPATHIC

Sleep Aid

1 FL OZ (30 ml)